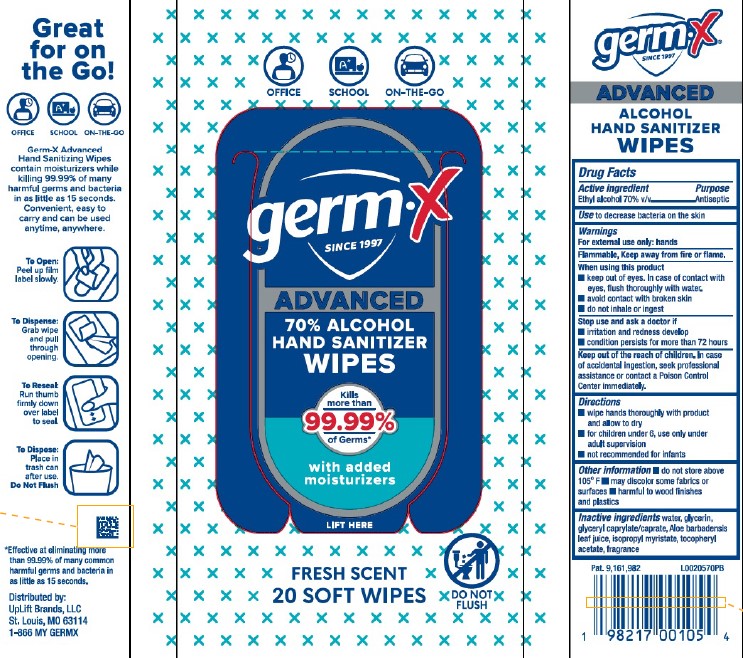 DRUG LABEL: Hand Sanitizing Wipes
NDC: 83986-028 | Form: CLOTH
Manufacturer: UpLift Brands LLC
Category: otc | Type: HUMAN OTC DRUG LABEL
Date: 20250612

ACTIVE INGREDIENTS: ALCOHOL 70 mL/100 mL
INACTIVE INGREDIENTS: WATER; GLYCERIN; GLYCERYL MONOCAPRYLOCAPRATE; ALOE VERA LEAF; ISOPROPYL MYRISTATE; .ALPHA.-TOCOPHEROL ACETATE

Germ-X D28.000/D28AA
Advanced Hand Sanitizer 70% Ethanol Wipe Solution

Claims

germ-x®

SINCE 1997

ADVANCED

ALCOHOL HAND SANITIZER WIPES

Active ingredient

Ethyl Alcohol 70% v/v

Purpose

Antiseptic

Use

to decrease bacteria on the skin

Warnings

For external use only: hands

Flammable, keep away from fire or flame.

When using this product

- keep out of eyes. In case of contact with eyes, flush thoroughly with water.
- avoid contact with broken skin
- do not inhale or ingest

Stop use and ask a doctor if

- irritation and redness develop
- condition persists for more than 72 hours

Keep out of reach of children.

In case of accidental ingestion, seek professional assistance or contact a Poison Control Center immediately.

Directions

- wipe hands thoroughly with product and allow to dry
- for children under 6, use only under adult supervision
- not recommended for infants

Other information

- do not store above 105ºF
- may discolor some fabrics or surfaces
- harmful to wood finishes and plastics

Inactive ingredients

water, glycerin, glyceryl caprylate/caprate, Aloe barbadensis leaf juice, isopropyl myristate, tocopheryl acetate, fragrance

Claims

Great for on the Go!

OFFICE

SCHOOL

ON-THE-GO

Germ-X Advanced Hand Sanitizing wipes contian moisturizers while killing 99.99% of many harmful germs and bacteria in as little as 15 seconds.

Convenient, easy to carry and can be used anytime, anywhere.

To Open: Peel up film label slowly.

To Dispense: Grab wipe and pull through opening.

To Reseal: Run thumb firmly down over label to seal.

To Dispose: Place in trash can after use.

Do Nut Flush

*Effective at eliminating more than 99.99% of many common harmful germs and bacteria in as little as 15 seconds.

Adverse reaction

Distributed by UpLift Brands, LLC

St. Louis, MO 36114

1-866-MY-GERMX

Pat. 9,161,982

Principal display panel

OFFICE

SCHOOL

ON-THE-GO

germ-X®

SINCE 1997

ADVANCED 70% ALCOHOL HAND SANITIZER WIPES

Kills more than 99.99% of Germs*

with added moisturizers

LIFT HERE

FRESH SCENT

20 SOFT WIPES

DO NOT FLUSH